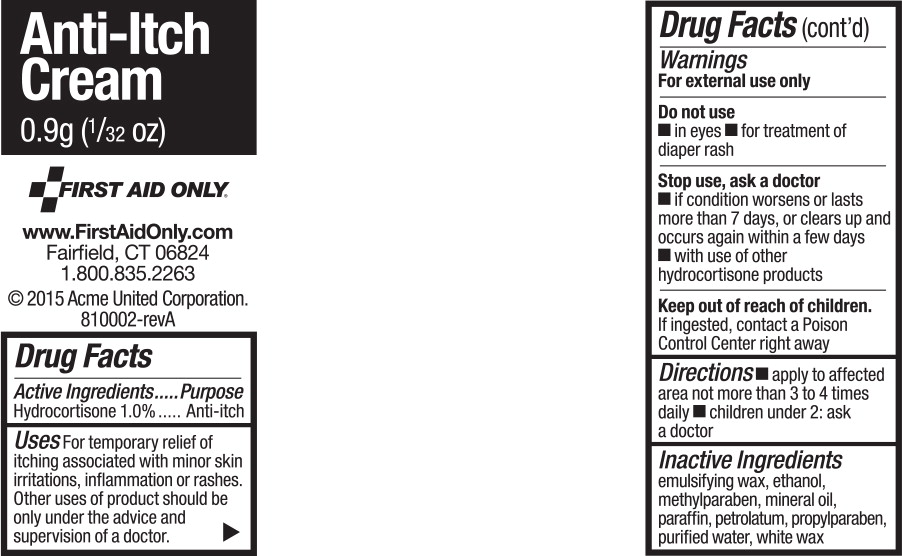 DRUG LABEL: Hydrocortisone
NDC: 62985-5125 | Form: CREAM
Manufacturer: First Aid Only, Inc
Category: otc | Type: HUMAN OTC DRUG LABEL
Date: 20150610

ACTIVE INGREDIENTS: Hydrocortisone 10 mg/1 g
INACTIVE INGREDIENTS: alcohol; methylparaben; mineral oil; paraffin; petrolatum; propylparaben; water; white wax

Drug Facts

Active Ingredients

Hydrocortisone 1.0%

Purpose

Anti-itch

Uses

For temporary relief of itching associated with minor skin irritations, inflammation or rashes. Other uses of product should be only under the advice and supervision of a doctor.

Warnings

For external use only

Do not use

- in eyes
- for treatment of diaper rash

Stop use, ask a doctor

- if condition worsens or lasts more than 7 days, or clears up and occurs again within a few days
- with use of other hydrocortisone products

Keep out of reach of children.

If ingested, contact a Poison Control Center right away

Directions

- apply to affected area not more than 3 to 4 times dally
- children under 2: ask a doctor

Inactive Ingredients

emulsifying wax, ethanol, methylparaben, mineral oil, paraffin, petrolatum, propylparaben, purified water, white wax

Principal Display Panel - Packet Label

Anti-Itch
Cream

0.9g (1/32 OZ)

FIRST AID ONLY.

www.FirstAidOnly.com

Fairfield, CT 06824

1.800.835.2263

© 2015 Acme United Corporation.

810002-revA